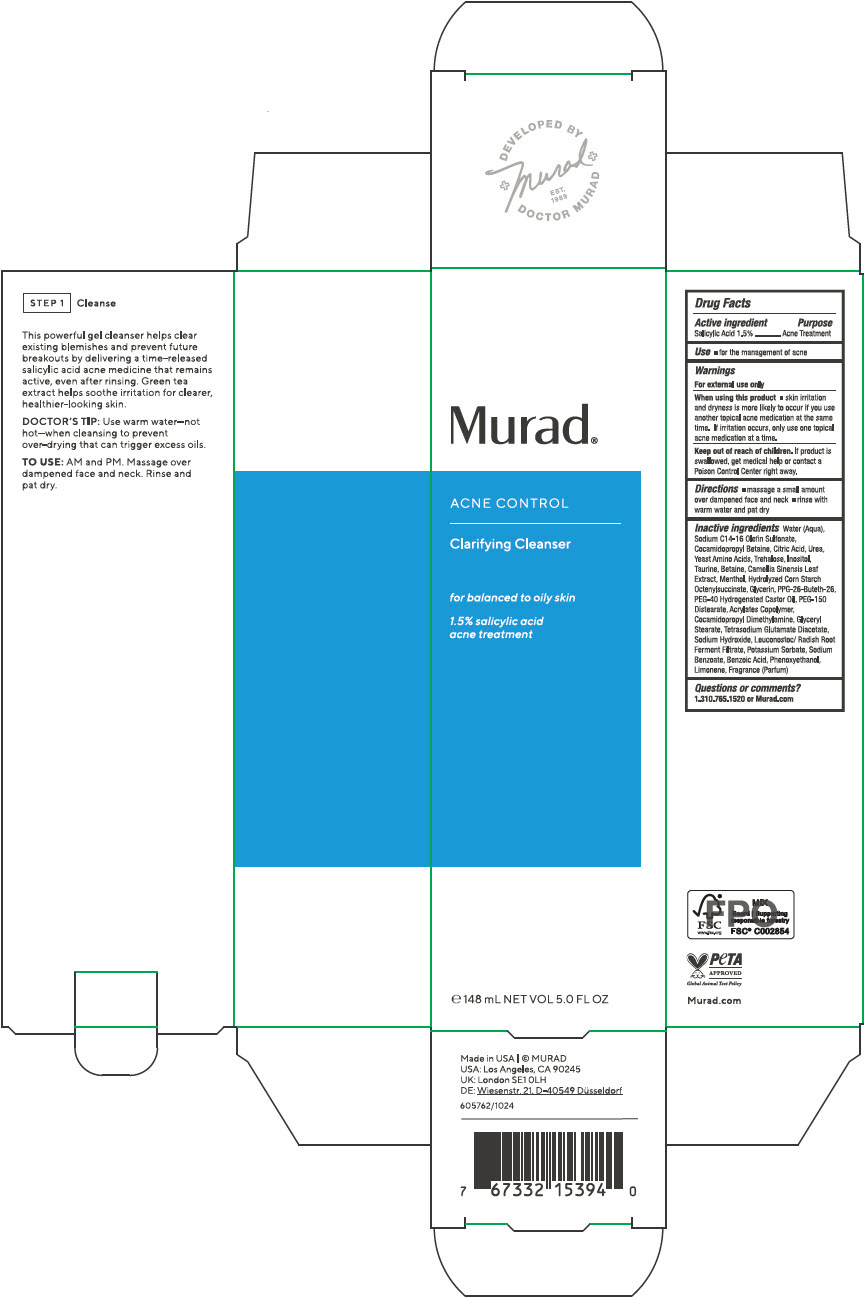 DRUG LABEL: Clarifying Cleanser
NDC: 70381-129 | Form: SOLUTION
Manufacturer: Murad, LLC
Category: otc | Type: HUMAN OTC DRUG LABEL
Date: 20250328

ACTIVE INGREDIENTS: SALICYLIC ACID 1.5 g/100 mL
INACTIVE INGREDIENTS: WATER; SODIUM C14-16 OLEFIN SULFONATE; COCAMIDOPROPYL BETAINE; CITRIC ACID MONOHYDRATE; UREA; AMINO ACIDS, SOURCE UNSPECIFIED; TREHALOSE; INOSITOL; TAURINE; BETAINE; GREEN TEA LEAF; MENTHOL, UNSPECIFIED FORM; STARCH, CORN; OCTENYLSUCCINIC ACID; GLYCERIN; PPG-26-BUTETH-26; POLYOXYL 40 HYDROGENATED CASTOR OIL; PEG-150 DISTEARATE; BUTYL ACRYLATE/METHYL METHACRYLATE/METHACRYLIC ACID COPOLYMER (18000 MW); COCAMIDOPROPYL DIMETHYLAMINE; GLYCERYL MONOSTEARATE; TETRASODIUM GLUTAMATE DIACETATE; SODIUM HYDROXIDE; LEUCONOSTOC/RADISH ROOT FERMENT FILTRATE; POTASSIUM SORBATE; SODIUM BENZOATE; BENZOIC ACID; PHENOXYETHANOL; LIMONENE, (+)-

Clarifying Cleanser

Drug Facts

Active ingredients

Salicylic Acid 1.5 %

Purpose

Acne Treatment

Use

- for the management of acne

Warnings

For external use only

When using this product

- skin irritation and dryness is more likely to occur if you use another topical acne medication at the same time. If irritation occurs, only use one topical acne medication at a time.

Keep out of reach of children. If product is swallowed, get medical help or contact a Poison Control Center right away.

Directions

- massage a small amount over dampened face and neck
- rinse with warm water and pat dry

Inactive ingredients

Water (Aqua), Sodium C14-16 Olefin Sulfonate, Cocamidopropyl Betaine, Citric Acid, Urea, Yeast Amino Acids, Trehalose, Inositol, Taurine, Betaine, Camellia Sinensis Leaf Extract, Menthol, Hydrolyzed Corn Starch Octenylsuccinate, Glycerin, PPG-26-Buteth-26, PEG-40 Hydrogenated Castor Oil, PEG-150 Distearate, Acrylates Copolymer, Cocamidopropyl Dimethylamine, Glyceryl Stearate, Tetrasodium Glutamate Diacetate, Sodium Hydroxide, Leuconostoc/Radish Root Ferment Filtrate, Potassium Sorbate, Sodium Benzoate, Benzoic Acid, Phenoxyethanol, Limonene, Fragrance (Parfum)

Questions or comments?

1.310.765.1520 or Murad.com

PRINCIPAL DISPLAY PANEL - 148 mL Tube Carton

Murad®

ACNE CONTROL

Clarifying Cleanser

for balanced to oily skin

1.5% salicylic acid
acne treatment

℮ 148 mL NET VOL 5.0 FL OZ